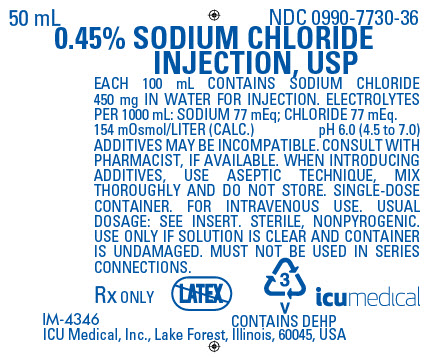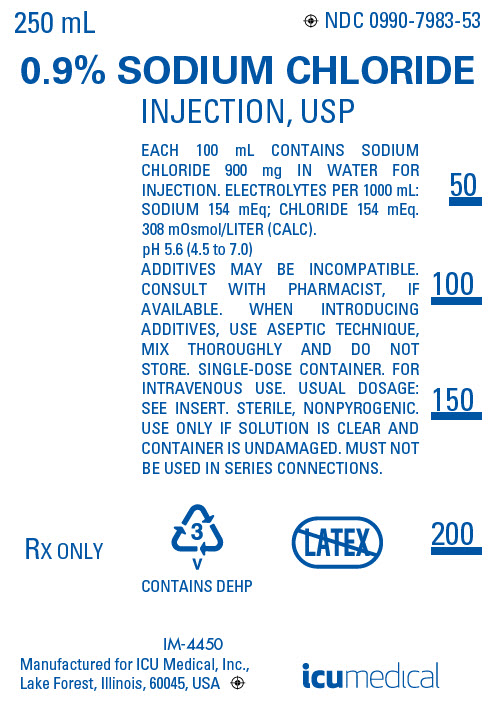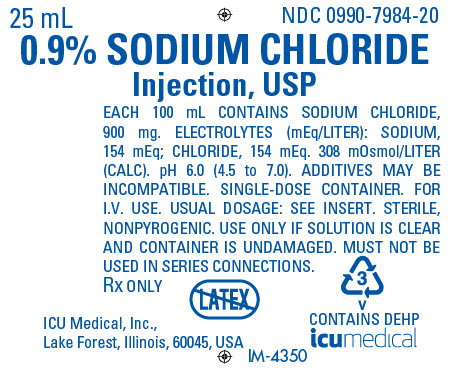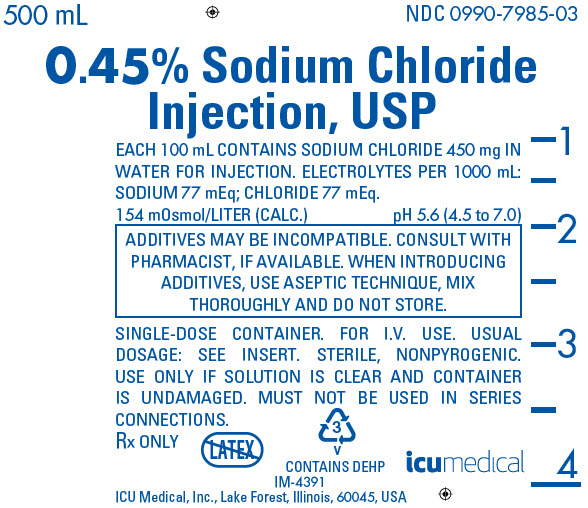 DRUG LABEL: Sodium Chloride
NDC: 0990-7730 | Form: INJECTION, SOLUTION
Manufacturer: ICU Medical Inc.
Category: prescription | Type: HUMAN PRESCRIPTION DRUG LABEL
Date: 20251102

ACTIVE INGREDIENTS: SODIUM CHLORIDE 450 mg/100 mL
INACTIVE INGREDIENTS: WATER

Sodium Chloride Injection, USP

Flexible Plastic Container Rx only

DESCRIPTION

Sodium Chloride Injection, USP solutions are sterile and nonpyrogenic. They are parenteral solutions containing various concentrations of sodium chloride in water for injection intended for intravenous administration.

For 0.45% Sodium Chloride Injection, USP, each 100 mL contains 450 mg sodium chloride in water for injection. Electrolytes per 1000 mL: sodium 77 mEq; chloride 77 mEq. The osmolarity is 154 mOsmol/L (calc.).

For 0.9% Sodium Chloride Injection, USP, each 100 mL contains 900 mg sodium chloride in water for injection. Electrolytes per 1000 mL: sodium 154 mEq; chloride 154 mEq. The osmolarity is 308 mOsmol/L (calc.).

The pH for both concentrations in the 100 mL and smaller containers is 6.0; for the 250 mL and larger containers, the pH is 5.6. The pH range is 4.5 to 7.0 for all containers.

The solutions contain no bacteriostat, antimicrobial agent or added buffer and each is intended only as a single-dose injection. When smaller doses are required the unused portion should be discarded.

The solutions are parenteral fluid and electrolyte replenishers.

Sodium Chloride, USP is chemically designated NaCl, a white crystalline powder freely soluble in water.

Water for Injection, USP is chemically designated H2O.

The flexible plastic container is fabricated from a specially formulated polyvinylchloride. Water can permeate from inside the container into the overwrap but not in amounts sufficient to affect the solution significantly. Solutions in contact with the plastic container may leach out certain chemical components from the plastic in very small amounts; however, biological testing was supportive of the safety of the plastic container materials. Exposure to temperatures above 25°C (77°F) during transport and storage will lead to minor losses in moisture content. Higher temperatures lead to greater losses. It is unlikely that these minor losses will lead to clinically significant changes within the expiration period.

CLINICAL PHARMACOLOGY

When administered intravenously, these solutions provide a source of water and electrolytes.

Solutions which provide combinations of hypotonic or isotonic concentrations of sodium chloride are suitable for parenteral maintenance or replacement of water and electrolyte requirements.

Isotonic concentrations of sodium chloride are suitable for parenteral replacement of chloride losses that exceed or equal the sodium loss. Hypotonic concentrations of sodium chloride are suited for parenteral maintenance of water requirements when only small quantities of salt are desired. A hypertonic concentration of sodium chloride may be used to repair severe salt depletion syndrome.

Sodium chloride in water dissociates to provide sodium (Na^+) and chloride (Cl^−) ions. Sodium (Na^+) is the principal cation of the extracellular fluid and plays a large part in the therapy of fluid and electrolyte disturbances. Chloride (Cl^−) has an integral role in buffering action when oxygen and carbon dioxide exchange occurs in the red blood cells. The distribution and excretion of sodium (Na^+) and chloride (Cl^−) are largely under the control of the kidney which maintains a balance between intake and output.

Water is an essential constituent of all body tissues and accounts for approximately 70% of total body weight. Average normal adult daily requirements range from two to three liters (1.0 to 1.5 liters each for insensible water loss by perspiration and urine production).

Water balance is maintained by various regulatory mechanisms. Water distribution depends primarily on the concentration of electrolytes in the body compartments and sodium (Na^+) plays a major role in maintaining physiologic equilibrium.

INDICATIONS AND USAGE

Intravenous solutions containing sodium chloride are indicated for parenteral replenishment of fluid and sodium chloride as required by the clinical condition of the patient.

CONTRAINDICATIONS

None known.

WARNINGS

Sodium Chloride Injection, USP should be used with great care, if at all, in patients with congestive heart failure, severe renal insufficiency and in clinical states in which there exists edema with sodium retention.

The intravenous administration of Sodium Chloride Injection, USP can cause fluid and/or solute overloading resulting in dilution of serum electrolyte concentrations, overhydration, congested states or pulmonary edema.

The risk of dilutive states is inversely proportional to the electrolyte concentration of the injections. The risk of solute overload causing congested states with peripheral and pulmonary edema is directly proportional to the electrolyte concentrations of the injections.

In patients with diminished renal function, administration of Sodium Chloride Injection, USP may result in sodium retention.

PRECAUTIONS

General

Do not use plastic containers in series connections. Such use could result in air embolism due to residual air being drawn from the primary container before administration of the fluid from the secondary container is completed.

Pressurizing intravenous solutions contained in flexible plastic containers to increase flow rates can result in air embolism if the residual air in the container is not fully evacuated prior to administration.

Use of a vented intravenous administration set with the vent in the open position could result in air embolism. Vented intravenous administration sets with the vent in the open position should not be used with flexible plastic containers.

Laboratory Tests

Clinical evaluation and periodic laboratory determinations are necessary to monitor changes in fluid balance, electrolyte concentrations and acid-base balance during prolonged parenteral therapy or whenever the condition of the patient warrants such evaluation.

DRUG INTERACTIONS

Caution must be exercised in the administration of Sodium Chloride Injection, USP to patients receiving corticosteroids or corticotropin.

Carcinogenesis, Mutagenesis, Impairment of Fertility

Studies have not been performed with Sodium Chloride Injection, USP to evaluate the potential for carcinogenesis, mutagenesis or impairment of fertility.

Pregnancy:

Teratogenic Effects

Pregnancy Category C

Animal reproduction studies have not been conducted with Sodium Chloride Injection, USP. It is also not known whether Sodium Chloride Injection, USP can cause fetal harm when administered to a pregnant woman or can affect reproduction capacity. Sodium Chloride Injection, USP should be given to a pregnant woman only if clearly needed.

Labor and Delivery

Studies have not been conducted to evaluate the effects of Sodium Chloride Injection, USP on labor and delivery. Caution should be exercised when administering this drug during labor and delivery.

Nursing Mothers

It is not known whether this drug is excreted in human milk. Because many drugs are excreted in human milk, caution should be exercised when Sodium Chloride Injection, USP is administered to a nursing mother.

Pediatric Use

The use of Sodium Chloride Injection, USP in pediatric patients is based on clinical practice.

Plasma electrolyte concentrations should be closely monitored in the pediatric population as this population may have impaired ability to regulate fluids and electrolytes.

The infusion of hypotonic fluids (0.45% Sodium Chloride Injection, USP) together with the non-osmotic secretion of ADH may result in hyponatremia in patients with acute volume depletion. Hyponatremia can lead to headache, nausea, seizures, lethargy, coma, cerebral edema and death, therefore acute symptomatic hyponatremic encephalopathy is considered a medical emergency.

Geriatric Use

Clinical studies of Sodium Chloride Injection, USP did not include sufficient numbers of subjects aged 65 and over to determine whether they respond differently from younger subjects. Other reported clinical experience has not identified differences in responses between elderly and younger patients. In general, dose selection for an elderly patient should be cautious, usually starting at the low end of the dosing range, reflecting the greater frequency of decreased hepatic, renal, or cardiac function, and of concomitant disease or drug therapy.

This drug is known to be substantially excreted by the kidney, and the risk of toxic reactions to this drug may be greater in patients with impaired renal function. Because elderly patients are more likely to have decreased renal function, care should be taken in dose selection, and it may be useful to monitor renal function.

Do not administer unless solution is clear and container is undamaged. Discard unused portion.

ADVERSE REACTIONS

Reactions which may occur because of the solution or the technique of administration include febrile response, infection at the site of injection, venous thrombosis or phlebitis extending from the site of injection, extravasation and hypervolemia.

If an adverse reaction does occur, discontinue the infusion, evaluate the patient, institute appropriate therapeutic countermeasures and save the remainder of the fluid for examination if deemed necessary.

In addition to the above listed adverse reactions hyponatremia has been reported for 0.45% Sodium Chloride Injection, USP (see Pediatric Use section).

OVERDOSAGE

In the event of overhydration or solute overload, re-evaluate the patient and institute appropriate corrective measures. (See WARNINGS, PRECAUTIONS, and ADVERSE REACTIONS.)

DOSAGE AND ADMINISTRATION

The dose is dependent upon the age, weight and clinical condition of the patient.

Additives may be incompatible. Consult with pharmacist, if available. When introducing additives, use aseptic technique, mix thoroughly and do not store.

Parenteral drug products should be inspected visually for particulate matter and discoloration prior to administration, whenever solution and container permit. (See PRECAUTIONS.)

INSTRUCTIONS FOR USE

To Open

Tear outer wrap at notch and remove solution container. If supplemental medication is desired, follow directions below before preparing for administration. Some opacity of the plastic due to moisture absorption during the sterilization process may be observed. This is normal and does not affect the solution quality or safety. The opacity will diminish gradually.

To Add Medication

1. Prepare additive port.
2. Using aseptic technique and an additive delivery needle of appropriate length, puncture resealable additive port at target area, inner diaphragm and inject. Withdraw needle after injecting medication.
3. The additive port may be protected by covering with an additive cap.
4. Mix container contents thoroughly.

Preparation for Administration

(Use aseptic technique)

1. Close flow control clamp of administration set.
2. Remove cover from outlet port at bottom of container.
3. Insert piercing pin of administration set into port with a twisting motion until the set is firmly seated. NOTE: See full directions on administration set carton.
4. Suspend container from hanger.
5. Squeeze and release drip chamber to establish proper fluid level in chamber.
6. Open flow control clamp and clear air from set. Close clamp.
7. Attach set to venipuncture device. If device is not indwelling, prime and make venipuncture.
8. Regulate rate of administration with flow control clamp.

WARNING: Do not use flexible container in series connections.

HOW SUPPLIED

Sodium Chloride Injection, USP is supplied in single-dose flexible plastic containers in various sizes and concentrations as shown in the accompanying Table.

NDC No. | Product | Container size mL
0409-7730-36 [Manufactured by ICU Medical, Inc., Lake Forest, Illinois, 60045, USA] | 0.45% Sodium Chloride Inj., USP | 50
0990-7730-36 | 0.45% Sodium Chloride Inj., USP | 50
0409-7730-37 | 0.45% Sodium Chloride Inj., USP | 100
0990-7730-37 | 0.45% Sodium Chloride Inj., USP | 100
0409-7985-02 | 0.45% Sodium Chloride Inj., USP | 250
0990-7985-02 | 0.45% Sodium Chloride Inj., USP | 250
0409-7985-03 [Manufactured for ICU Medical, Inc., Lake Forest, Illinois, 60045, USA] | 0.45% Sodium Chloride Inj., USP | 500
0990-7985-03, | 0.45% Sodium Chloride Inj., USP | 500
0409-7985-09, | 0.45% Sodium Chloride Inj., USP | 1000
0990-7985-09, | 0.45% Sodium Chloride Inj., USP | 1000
0409-7984-20 | 0.9% Sodium Chloride Inj., USP | 25
0990-7984-20 | 0.9% Sodium Chloride Inj., USP | 25
0409-7984-36 | 0.9% Sodium Chloride Inj., USP | 50
0990-7984-36 | 0.9% Sodium Chloride Inj., USP | 50
0409-7984-13 | 0.9% Sodium Chloride Inj., USP | 50
0990-7984-13 | 0.9% Sodium Chloride Inj., USP | 50
0409-7984-37 | 0.9% Sodium Chloride Inj., USP | 100
0990-7984-37 | 0.9% Sodium Chloride Inj., USP | 100
0409-7984-23 | 0.9% Sodium Chloride Inj., USP | 100
0990-7984-23 | 0.9% Sodium Chloride Inj., USP | 100
0409-7983-61 | 0.9% Sodium Chloride Inj., USP | 150
0990-7983-61 | 0.9% Sodium Chloride Inj., USP | 150
0409-7983-02, | 0.9% Sodium Chloride Inj., USP | 250
0990-7983-02, | 0.9% Sodium Chloride Inj., USP | 250
0409-7983-53 | 0.9% Sodium Chloride Inj., USP | 250
0990-7983-53 | 0.9% Sodium Chloride Inj., USP | 250
0409-7983-03 | 0.9% Sodium Chloride Inj., USP | 500
0990-7983-03, | 0.9% Sodium Chloride Inj., USP | 500
0409-7983-55 | 0.9% Sodium Chloride Inj., USP | 500
0990-7983-55 | 0.9% Sodium Chloride Inj., USP | 500
0409-7983-09, | 0.9% Sodium Chloride Inj., USP | 1000
0990-7983-09, | 0.9% Sodium Chloride Inj., USP | 1000

ICU Medical is transitioning NDC codes from "0409" to "0990" labeler code. Both NDC codes are expected to be in the market for a period of time.

Store at 20 to 25°C (68 to 77°F). [See USP Controlled Room Temperature.] Protect from freezing.

Revised: April, 2020

IFU0000188

PRINCIPAL DISPLAY PANEL - 50 mL Bag Label

50 mL
NDC 0990-7730-36

0.45% SODIUM CHLORIDE
INJECTION, USP

EACH 100 mL CONTAINS SODIUM CHLORIDE
450 mg IN WATER FOR INJECTION. ELECTROLYTES
PER 1000 mL: SODIUM 77 mEq; CHLORIDE 77 mEq.
154 mOsmol/LITER (CALC.) pH 6.0 (4.5 to 7.0)
ADDITIVES MAY BE INCOMPATIBLE. CONSULT WITH
PHARMACIST, IF AVAILABLE. WHEN INTRODUCING
ADDITIVES, USE ASEPTIC TECHNIQUE, MIX
THOROUGHLY AND DO NOT STORE. SINGLE-DOSE
CONTAINER. FOR INTRAVENOUS USE. USUAL
DOSAGE: SEE INSERT. STERILE, NONPYROGENIC.
USE ONLY IF SOLUTION IS CLEAR AND CONTAINER
IS UNDAMAGED. MUST NOT BE USED IN SERIES
CONNECTIONS.

Rx ONLY

3
v
CONTAINS DEHP

IM-4346

ICU Medical, Inc., Lake Forest, Illinois, 60045, USA

icumedical

PRINCIPAL DISPLAY PANEL - 250 mL Bag Label

250 mL
NDC 0990-7983-53

0.9% SODIUM CHLORIDE
INJECTION, USP

EACH 100 mL CONTAINS SODIUM
CHLORIDE 900 mg IN WATER FOR
INJECTION. ELECTROLYTES PER 1000 mL:
SODIUM 154 mEq; CHLORIDE 154 mEq.
308 mOsmol/LITER (CALC).
pH 5.6 (4.5 to 7.0)
ADDITIVES MAY BE INCOMPATIBLE.
CONSULT WITH PHARMACIST, IF
AVAILABLE. WHEN INTRODUCING
ADDITIVES, USE ASEPTIC TECHNIQUE,
MIX THOROUGHLY AND DO NOT
STORE. SINGLE-DOSE CONTAINER. FOR
INTRAVENOUS USE. USUAL DOSAGE:
SEE INSERT. STERILE, NONPYROGENIC.
USE ONLY IF SOLUTION IS CLEAR AND
CONTAINER IS UNDAMAGED. MUST NOT
BE USED IN SERIES CONNECTIONS.

Rx ONLY

3
v
CONTAINS DEHP

IM-4450

Manufactured for ICU Medical, Inc.,
Lake Forest, Illinois, 60045, USA

icumedical

PRINCIPAL DISPLAY PANEL - 25 mL Bag Label

25 mL
NDC 0990-7984-20

0.9% SODIUM CHLORIDE
Injection, USP

EACH 100 mL CONTAINS SODIUM CHLORIDE,
900 mg. ELECTROLYTES (mEq/LITER): SODIUM,
154 mEq; CHLORIDE, 154 mEq. 308 mOsmol/LITER
(CALC). pH 6.0 (4.5 to 7.0). ADDITIVES MAY BE
INCOMPATIBLE. SINGLE-DOSE CONTAINER. FOR
I.V. USE. USUAL DOSAGE: SEE INSERT. STERILE,
NONPYROGENIC. USE ONLY IF SOLUTION IS CLEAR
AND CONTAINER IS UNDAMAGED. MUST NOT BE
USED IN SERIES CONNECTIONS.

Rx ONLY

3
v
CONTAINS DEHP

ICU Medical, Inc.,
Lake Forest, Illinois, 60045, USA

icumedical

IM-4350

PRINCIPAL DISPLAY PANEL - 500 mL Bag Label

500 mL
NDC 0990-7985-03

0.45% Sodium Chloride
Injection, USP

EACH 100 mL CONTAINS SODIUM CHLORIDE 450 mg IN
WATER FOR INJECTION. ELECTROLYTES PER 1000 mL:
SODIUM 77 mEq; CHLORIDE 77 mEq.

154 mOsmol/LITER (CALC.)
pH 5.6 (4.5 to 7.0)

ADDITIVES MAY BE INCOMPATIBLE. CONSULT WITH
PHARMACIST, IF AVAILABLE. WHEN INTRODUCING
ADDITIVES, USE ASEPTIC TECHNIQUE, MIX
THOROUGHLY AND DO NOT STORE.

SINGLE-DOSE CONTAINER. FOR I.V. USE. USUAL
DOSAGE: SEE INSERT. STERILE, NONPYROGENIC.
USE ONLY IF SOLUTION IS CLEAR AND CONTAINER
IS UNDAMAGED. MUST NOT BE USED IN SERIES
CONNECTIONS.

Rx ONLY

3
v
CONTAINS DEHP

icumedical

IM-4391

ICU Medical, Inc., Lake Forest, Illinois, 60045, USA